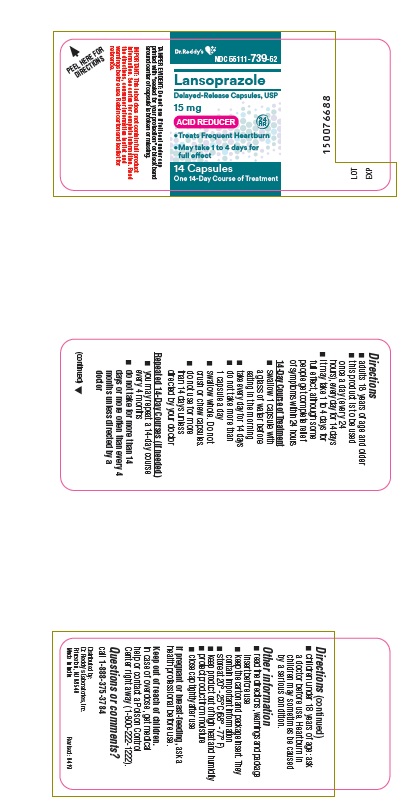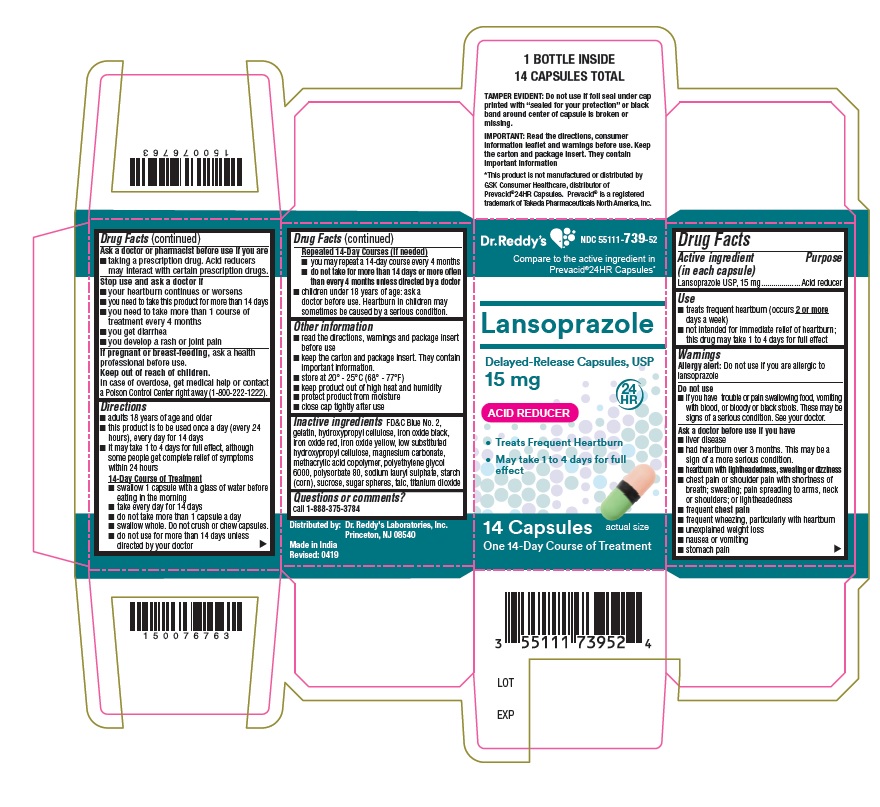 DRUG LABEL: Lansoprazole
NDC: 55111-739 | Form: CAPSULE, DELAYED RELEASE
Manufacturer: Dr. Reddy's Laboratories Limited
Category: otc | Type: HUMAN OTC DRUG LABEL
Date: 20250703

ACTIVE INGREDIENTS: Lansoprazole 15 mg/1 1
INACTIVE INGREDIENTS: FD&C BLUE NO. 2; FERRIC OXIDE RED; FERRIC OXIDE YELLOW; GELATIN; HYDROXYPROPYL CELLULOSE (110000 WAMW); FERROSOFERRIC OXIDE; Hydroxypropyl Cellulose, Low Substituted; MAGNESIUM CARBONATE; METHACRYLIC ACID - ETHYL ACRYLATE COPOLYMER (1:1) TYPE A; POLYETHYLENE GLYCOL 6000; POLYSORBATE 80; SODIUM LAURYL SULFATE; STARCH, CORN; SUCROSE; TALC; TITANIUM DIOXIDE

Lansoprazole Delayed Release Capsules USP

Active ingredient (in each capsule)

Lansoprazole USP, 15 mg

Purpose

Acid reducer

Use

- treats frequent heartburn (occurs 2 or more days a week)
- not intended for immediate relief of heartburn; this drug may take 1 to 4 days for full effect

Warnings

Allergy alert: Do not use if you are allergic to lansoprazole

Do not use

- if you have trouble or pain swallowing food, vomiting with blood, or bloody or black stools.These may be signs of a serious condition. See your doctor.

Ask a doctor before use if you have

- liver disease
- had heartburn over 3 months. This may be a sign of a more serious condition.
- heartburn with lightheadedness, sweating or dizziness
- chest pain or shoulder pain with shortness of breath; sweating; pain spreading to arms, neck or shoulders; or lightheadedness
- frequent chest pain
- frequent wheezing, particularly with heartburn
- unexplained weight loss
- nausea or vomiting
- stomach pain

Ask a doctor or pharmacist before use if you are

- taking a prescription drug. Acid reducers may interact with certain prescription drugs.

Stop use and ask a doctor if

- your heartburn continues or worsens
- you need to take this product for more than 14 days
- you need to take more than 1 course of treatment every 4 months
- you get diarrhea
- you develop a rash or joint pain

If pregnant or breast-feeding,

ask a healthcare professional before use.

Keep out of reach of children.

In case of overdose, get medical help or contact a Poison Control Center right away. (1-800-222-1222)

Directions

- adults 18 years of age and older
- this product is to be used once a day (every 24 hours), every day for 14 days
- it may take 1 to 4 days for full effect, although some people get complete relief of symptoms within 24 hours

14-Day Course of Treatment

- swallow 1 capsule with a glass of water before eating in the morning
- take every day for 14 days
- do not take more than 1 capsule a days
- swallow whole. Do not crush or chew capsules.
- do not use for more than 14 days unless directed by your doctor

Repeated 14-Day Courses (if needed)

- you may repeat a 14-day course every 4 months
- do not take for more than 14 days or more often than every 4 months unless directed by a doctor
- children under 18 years of age: ask a doctor before use. Heartburn in children may sometimes be caused by a serious condition.

Other information

- read the directions, warnings and package insert before use
- keep the carton and package insert. They contain important information.
- store at 20 – 25°C (68° – 77° F)
- keep product out of high heat and humidity
- protect product from moisture
- close cap tightly after use

Inactive ingredients

FD&C Blue No. 2, gelatin, hydroxypropyl cellulose, iron oxide black, iron oxide red, iron oxide yellow, low substituted hydroxypropyl cellulose, magnesium carbonate, methacrylic acid copolymer, polyethylene glycol 6000, polysorbate 80, sodium lauryl sulphate, starch (corn), sucrose, sugar spheres, talc, titanium dioxide

Questions or comments?

call 1-888-375-3784

Consumer Information

Lansoprazole Delayed-Release Capsules USP, 15 mg / Acid Reducer

• Treats Frequent Heartburn

• May take 1 to 4 days for full effect

Please read the entire package insert before taking Lansoprazole Delayed-Release Capsules USP, 15 mg. Save for future reference.

How Lansoprazole Delayed-Release Capsules USP, 15 mg Treat Your Frequent Heartburn

Lansoprazole Delayed-Release Capsules USP, 15 mg stops acid production at the source - the pumps that release acid into the stomach. Lansoprazole Delayed-Release Capsules USP, 15 mg is taken once a day (every 24 hours), every day for 14 days.

What You Can Expect When Taking Lansoprazole Delayed-Release Capsules USP, 15 mg

Frequent heartburn can occur anytime during the 24-hour period (day or night). Take Lansoprazole Delayed-Release Capsules USP, 15 mg in the morning before eating. Lansoprazole Delayed-Release Capsules USP, 15 mg is clinically proven to treat frequent heartburn. Although some people get complete relief of symptoms within 24 hours, it may take 1 to 4 days for full effect. Make sure you take Lansoprazole Delayed-Release Capsules USP, 15 mg every day for 14 days to treat your frequent heartburn.

Who Should Take Lansoprazole Delayed-Release Capsules USP, 15 mg

Adults (18 years and older) with frequent heartburn - when you have heartburn 2 or more days a week.

Who Should NOT Take Lansoprazole Delayed-Release Capsules USP, 15 mg

People who have one episode of heartburn a week or less, or who want immediate relief of heartburn.

How To take Lansoprazole Delayed-Release Capsules USP, 15 mg

14-DAY Course of Treatment

• Swallow 1 capsule with a glass of water before eating in the morning.

• Take every day for 14 days.

• Do not take more than 1 capsule a day.

• Swallow whole. Do not crush or chew capsules.

• Do not use for more than 14 days unless directed by your doctor.

When to Take Lansoprazole Delayed-Release Capsules USP, 15 mg Again.

You may repeat a 14-day course of therapy every 4 months.

When to Talk To Your Doctor

Do not take for more than 14 days or more often than every 4 months unless directed by a doctor.

Warnings And When to Ask Your Doctor

Allergy alert: Do not use if you are allergic to lansoprazole

Do not use

• if you have trouble or pain swallowing food, vomiting with blood, or bloody or black stools. These may be signs of a serious condition. See your doctor.

Ask a doctor before use if you have

• liver disease

• had heartburn over 3 months. This may be a sign of a more serious condition.

• heartburn with lightheadedness, sweating or dizziness

• chest pain or shoulder pain with shortness of breath; sweating; pain spreading to arms, neck or shoulders; or lightheadedness

• frequent chest pain

• frequent wheezing, particularly with heartburn

• unexplained weight loss

• nausea or vomiting

• stomach pain

Ask a doctor or pharmacist before use if you are

• taking a prescription drug. Acid reducers may interact with certain prescription drugs.

Stop use and ask a doctor if

• your heartburn continues or worsens

• you need to take this product for more than 14 days

• you need to take more than 1 course of treatment every 4 months

• you get diarrhea

• you develop a rash or joint pain

If pregnant or breast-feeding, ask a health professional before use.

Keep out of reach of children. In case of overdose, get medical help or contact a Poison Control Center right away. (1-800-222-1222)

Tips For Managing Heartburn

• Avoid foods or drinks that are more likely to cause heartburn, such as rich, spicy, fatty and fried foods, chocolate, caffeine, alcohol and even some acidic fruits and vegetables.

• Eat slowly and do not eat big meals.

• Do not eat late at night or just before bedtime.

• Do not lie flat or bend over soon after eating.

• Raise the head of your bed.

• Wear loose-fitting clothing around your stomach.

• If you are overweight, lose weight.

• If you smoke, quit smoking.

Clinical studies prove Lansoprazole Delayed-Release Capsules USP, 15 mg effectively treat frequent heartburn

In three clinical studies, Lansoprazole Delayed-Release Capsules USP, 15 mg was shown to be significantly better than placebo in treating frequent heartburn.

How Lansoprazole Delayed-Release Capsules USP, 15 mg is Sold

Lansoprazole Delayed-Release Capsules USP, 15 mg are available in 14 capsule, 28 capsule and 42 capsule sizes. These sizes contain one, two and three 14-day courses of treatment, respectively. Do not use for more than 14 days in a row unless directed by your doctor. For the 28 count (two 14-day courses) and the 42 count (three 14-day courses), you may repeat a 14-day course every 4 months.

For Questions or Comments About Lansoprazole Delayed-Release Capsules USP, 15 mg

Call 1-888-375-3784

Manufactured by:

Dr. Reddy's Laboratories Limited

Bachupally - 500 090 INDIA

Principal Display Panel

Container : 14's count

Principal Display Panel

Container carton : 14's count